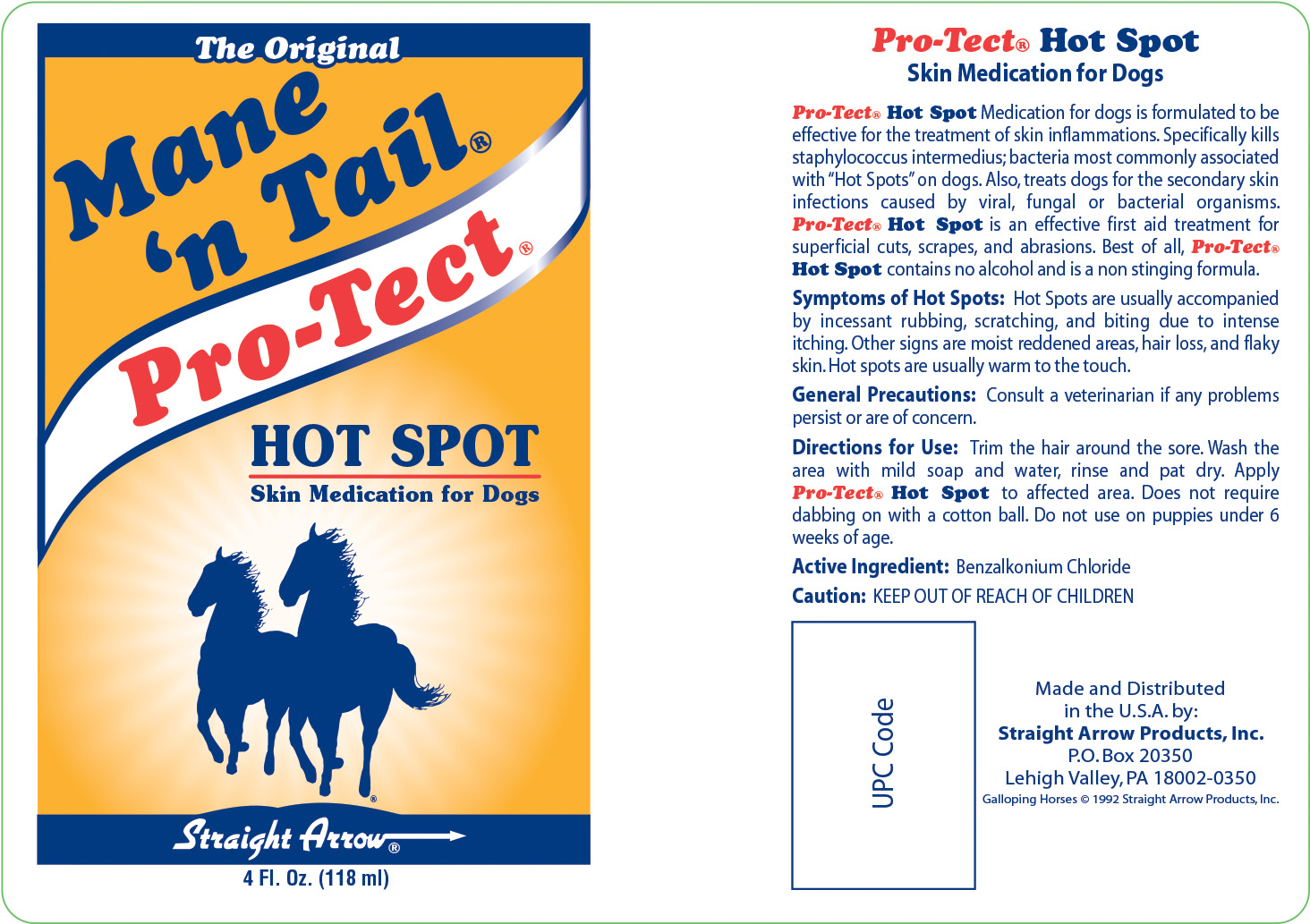 DRUG LABEL: Pro-Tect Hot Spot Skin Medication
NDC: 62001-0317 | Form: LIQUID
Manufacturer: Straight Arrow Products, Inc.
Category: animal | Type: OTC ANIMAL DRUG LABEL
Date: 20250702

ACTIVE INGREDIENTS: BENZALKONIUM CHLORIDE .001 g/1 g
INACTIVE INGREDIENTS: WATER; PROPYLENE GLYCOL; COCAMIDOPROPYL BETAINE; HYPROMELLOSES; CETRIMONIUM CHLORIDE; IMIDUREA; DIDECYLDIMONIUM CHLORIDE; OCTOXYNOL 9; QUATERNIUM-15; METHYLPARABEN; ANHYDROUS CITRIC ACID; ALLANTOIN; PROPYLPARABEN; D&C GREEN NO. 5; TROLAMINE

Active Ingredient:

Benzalkonium chloride

Purpose:

Purpose: Pro-Tect Hot Spot Medication for dogs is formulated to be effective for the treatment of skin inflammations. Specifically kills staphylococcus intermedius; bacteria most commonly associated with "Hot Spots" on dogs. Also, treats dogs for the secondary skin infections caused by viral, fungal or bacterial organisms. Pro-Tect Hot Spot is an effective first aid treatment for superficial cuts, scrapes, and abrasions. Best of all, Pro-Tect Hot Spot contains no alcohol and is a non-stinging formula.
Symptons of Hot Spots: Hot Spots are usually accompanied by incessant rubbing, scratching, and biting due to intense itching. Other signs are moist reddened areas, hair loss, and flaky skin. Hot spots are usually warm to the touch.

Directions for Use:

Trim the hair around the sore. Wash the area with mild soap and water, rinse and pat dry. Apply Pro-Tect Hot Spot to affected area. Does not require dabbing on with a cotton ball. Do not use on puppies under 6 weeks of age.

General Precautions:

Consult a veterinarian if any problems persist or are of concern.

Caution: KEEP OUT OF REACH OF CHILDREN